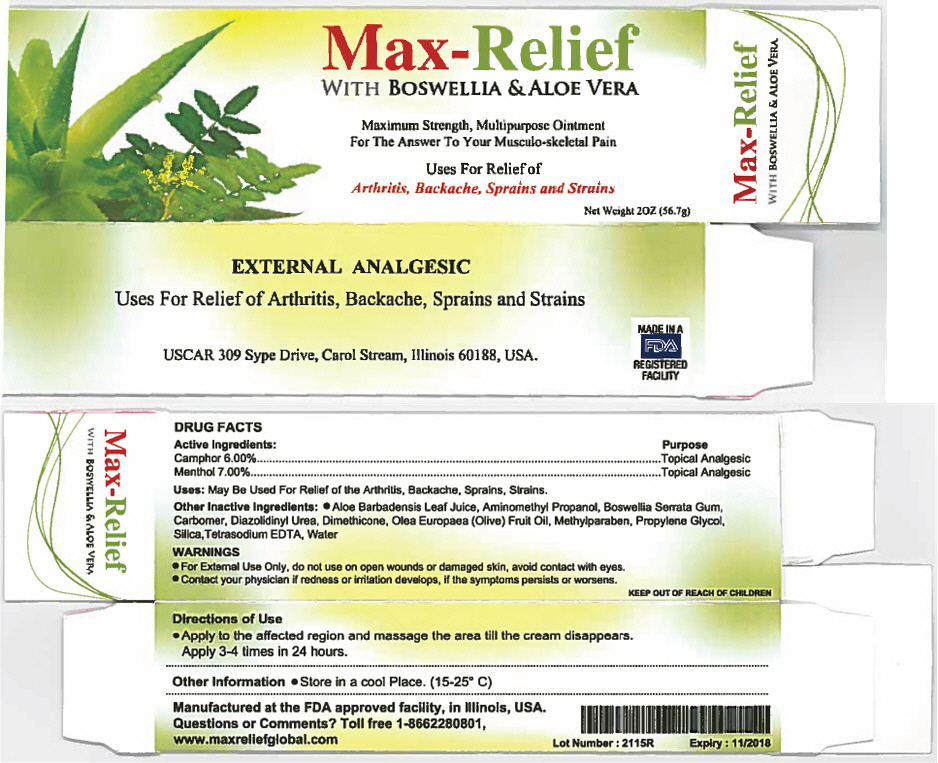 DRUG LABEL: Max-Relief with Boswellia and Aloe Vera
NDC: 71473-067 | Form: GEL
Manufacturer: USConsultancy for Applied Research
Category: otc | Type: HUMAN OTC DRUG LABEL
Date: 20200110

ACTIVE INGREDIENTS: Menthol, Unspecified Form 7 g/100 g; Camphor (Synthetic) 6 g/100 g
INACTIVE INGREDIENTS: Aloe Vera Leaf; Aminomethylpropanol; Indian Frankincense; Carboxypolymethylene; Diazolidinyl Urea; Dimethicone; Olive Oil; Methylparaben; Propylene Glycol; Silicon Dioxide; Edetate Sodium; Water

Max-Relief with Boswellia & Aloe Vera

Drug Facts:

ACTIVE INGREDIENT

Active Ingredients: | Purpose
Camphor 6.00% | Topical Analgesic
Menthol 7.00% | Topical Analgesic

Uses

May Be Used For Relief of the Arthritis, Backache, Sprains, Strains

Other inactive ingredients

Aloe Barbadensis Leaf Juice, Aminomethyl Propanol, Boswellia Serrata Gum, Carbomer, Diazolidinyl Urea, Dimethicone, Olea Europaea (Olive) Fruit Oil, MethylParaben, Propylene Glycol, Silica, Tetrasodium EDTA, Water

Warnings

- For External Use Only! Do not use on open wounds or damaged skin. Avoid contact with eyes. Contact your physician if redness or irritation develops or if the symptoms persist or worsen.

KEEP OUT OF REACH OF CHILDREN

Directions of Use

- Apply to the affected region and massage the area till the cream disappears. Apply 3-4 times in 24 hours.

Other Information

Store in a cool place (15-25° C)

Questions or comments

Toll Free 1-866-222-80801
www.maxreliefglobal.com

PRINCIPAL DISPLAY PANEL - 56.7 g Tube Carton

Max-Relief
WITH BOSWELLIA & ALOE VERA

Maximum Strength, Multipurpose Ointment
For The Answer To Your Musculo-skeletal Pain

Uses For Relief of
Arthritis, Backache, Sprains and Strains

Net Weight 2OZ (56.7g)